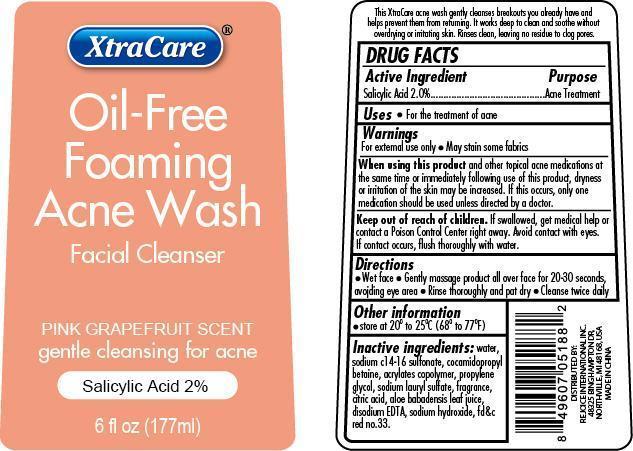 DRUG LABEL: Oil-Free Foaming Acne Wash Facial Cleanser
NDC: 57337-033 | Form: GEL
Manufacturer: Rejoice International
Category: otc | Type: HUMAN OTC DRUG LABEL
Date: 20240228

ACTIVE INGREDIENTS: SALICYLIC ACID 4 mg/177 mg
INACTIVE INGREDIENTS: WATER; SODIUM C14-16 OLEFIN SULFONATE; COCAMIDOPROPYL BETAINE; CARBOMER COPOLYMER TYPE A (ALLYL PENTAERYTHRITOL CROSSLINKED); PROPYLENE; SODIUM LAURYL SULFATE; CITRIC ACID MONOHYDRATE; ALOE VERA LEAF; EDETATE DISODIUM; SODIUM HYDROXIDE; D&C RED NO. 33

Oil-Free Foaming Acne Wash Facial Cleanser

Active Ingredient Purpose

Salicylic Acid 2.0% ............................. Acne Treatment

PURPOSE

XtraCare Oil-Free Foaming Acne Wash Facial Cleanser

PINK GRAPEFRUIT SCENT

gentle cleansing for acne

Salicylic Acid 2%

Keep out of reach of children. If swallowed, get medical help or contact a Poison Control Center right away. Avoid contact with eyes. If contact occurs, flush thoroughly with water.

INDICATIONS AND USAGE

This XtraCare acne wash gently cleanses breakouts you already have and helps prevent them from returning. It works deep to clean and soothe without overdrying or irritating skin. Rinses clean, leaving no residue to clog pores.

Warnings

For external use only.

May stain some fabrics

When using this product and other topical acne medications at the same time or immediately following use of this product, dryness or irritation of the skin may be increased. If this occurs, only one medication should be used unless directed by a doctor.

Directions

Wet face. Gently massage product all over face for 20-30 seconds, avoiding eye area. Rinse thoroughly and pat dry. Cleanse twice daily

INACTIVE INGREDIENT

Inactive Ingredients: water, sodium c14-16 olefin sulfonate, cocamidopropyl betaine, acrylates copolymer, propylene glycol, sodium lauryl sulfate, fragrance, citric acid, aloe barbadensis leaf juice, disodium EDTA, sodium hydroxide, fd&c red no.33

Other information

store at 20o to 25oC (68o to 77oF)

DISTRIBUTED BY

REJOICE INTERNATIONAL INC

48325 BINGHAMPTON DR

NORTHVILLE, MI 48168 USA

MADE IN CHINA